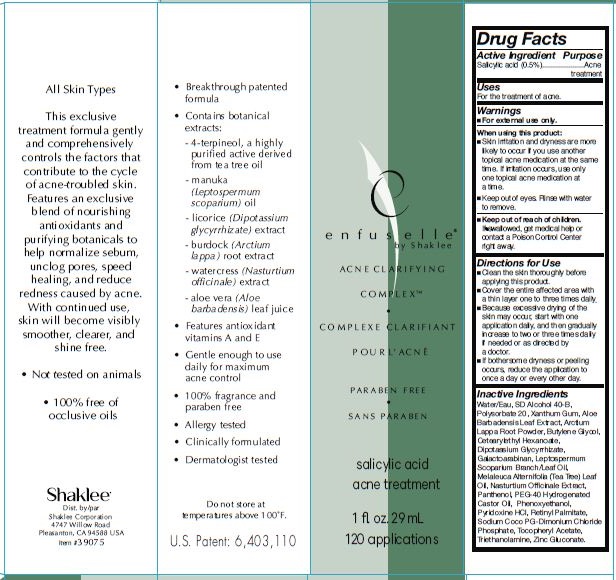 DRUG LABEL: enfuselle Acne Clarifying
NDC: 59899-002 | Form: LOTION
Manufacturer: Shaklee Corporation
Category: otc | Type: HUMAN OTC DRUG LABEL
Date: 20231103

ACTIVE INGREDIENTS: SALICYLIC ACID 5 mg/1 mL
INACTIVE INGREDIENTS: WATER; XANTHAN GUM; 4-TERPINEOL, (+/-)-; TROLAMINE; GALACTOARABINAN; ZINC GLUCONATE; MANUKA OIL; .ALPHA.-TOCOPHEROL ACETATE; GLYCYRRHIZINATE DIPOTASSIUM; PANTHENOL; EDETATE DISODIUM; CETEARYL ETHYLHEXANOATE; BUTYLENE GLYCOL; NASTURTIUM OFFICINALE; ARCTIUM LAPPA ROOT; ALOE VERA LEAF; PYRIDOXINE HYDROCHLORIDE; VITAMIN A PALMITATE

enfuselle ACNE CLARIFYING COMPLEX

Active Ingredient

Salicylic Acid (0.5%)

Purpose

Acne treatment

Uses

For the treatment of acne.

Warnings

- For external use only.

When using this product

- Skin irritation and dryness are more likely to occur if you use another topical acne medication at the same time. If irritation occurs, use only one topical acne medication at a time.
- Keep out of eyes. Rinse with water to remove.

Keep out of reach of children.

In swallowed, get medical help or contact a Poison Control Center right away.

Directions for Use

- Clean the skin thoroughly before applying this product.
- Cover the entire affected area with a thin layer one to three times daily.
- Because excessive drying of the skin may occur, start with one application daily, then gradually increase to two or three times daily if needed or as directed by a doctor.
- If bothersome dryness or peeling occurs, reduce application to once a day or every other day.

INACTIVE INGREDIENTS

Water/Eau, SD Alcohol 40-B, Cyclodextrin, Polysorbate 20, Xanthan Gum, 4-Terpineol*, Triethanolamine, Galactoarabinan, Zinc Gluconate, Sodium Coco PG-Dimonium Chloride Phosphate, Leptospermum Scoparium Branch/Leaf Oil, Tocopheryl Acetate, Dipostassium Glycyrrhizate, Panthenol, Disodium EDTA, Cetearyl Ethylhexanoate, Butylene Glycol, Nasturtium Officinale Extract, Arctium Lappa Root Extract, Aloe Barbadensis Leaf Juice, Pyridoxine HCL, Retinyl Palmitate.

Principal Labeling

PARABEN FREE

salicylic acid acne treatment

1fl. oz. 29mL 120applications

All Skin Types

This exclusive treatment formula gently and comprehensively controls the factors that contribute to the cycle of acne-troubled skin. Features an exclusive blend of nourishing antioxidants and purifying botanicals to help normalize sebum, unclog pores, speed healing, and reduce redness caused by acne. With continued use, skin will become visibly smoother, clearer, and shine free.

Shaklee Dist. by/par Shaklee Corporation 4747 Willow Road Pleasanton, CA 94588 USA Item #39075

• Breakthrough patented formula • Contains botanical extracts: - tea tree (Melaleuca alternifolia) oil - manuka (Leptospermum scoparium) oil - licorice (Dipotassium glycyrrhizate) extract - burdock (Arctium lappa) root extract - watercress (Nasturtium officinale) extract - aloe vera (Aloe barbadensis) leaf juice • Features antioxidant vitamins A and E • Gentle enough to use daily for maximum acne control • 100% fragrance and paraben free • Allergy tested • Clinically formulated • Dermatologist tested

Do not store at temperatures above 10O°F. U.S. Palent: 6,403,110

Apply this exclusive facial formula to help keep skin blemish free, speed healing and reduce redness caused by acne. Gentle enough to use daily, this unique blend of botanicals and nourishing antioxidants effectively controls the factors that contribute to the cycle of acnetroubled skin.

WARNINGS: For external use only. Keep out of eyes. “Keep out of reach of children. If excessive dryness or peeling occurs, reduce the application to once a day or every other day.

Directions: Apply one to three times daily after cleansing and toning. Allow to dry after application. Follow with the Enfuselle treatment or moisturizer for your skin type.

- Not tested on animals
- 100% free of occlusive oils